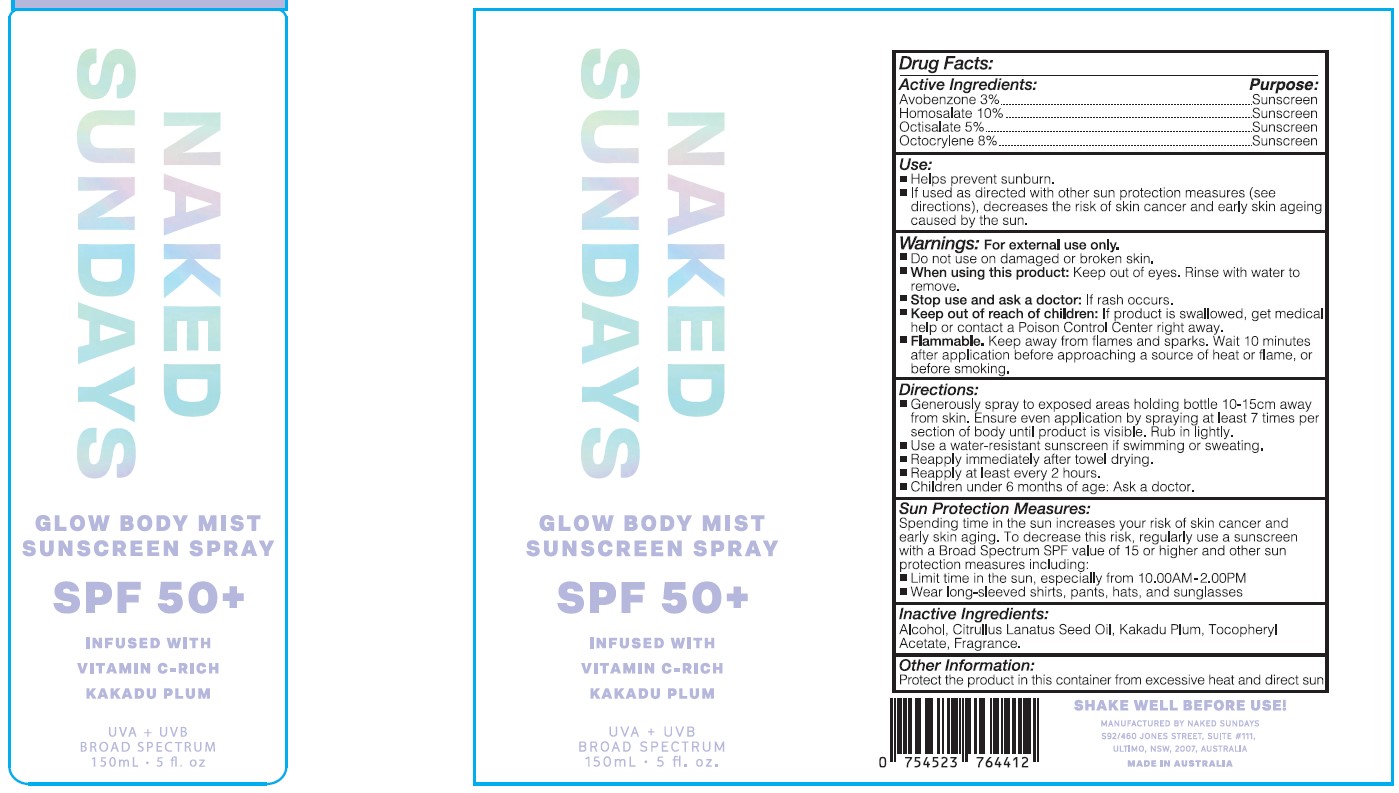 DRUG LABEL: GLOW BODY MIST

NDC: 81104-110 | Form: SPRAY
Manufacturer: NAKED SUNDAYS PTY LTD
Category: otc | Type: HUMAN OTC DRUG LABEL
Date: 20250323

ACTIVE INGREDIENTS: OCTOCRYLENE 10.5 g/100 mL; AVOBENZONE 4.5 g/100 mL; HOMOSALATE 15 g/100 mL; OCTISALATE 7.5 g/100 mL
INACTIVE INGREDIENTS: KAKADU PLUM; ALCOHOL; WATERMELON SEED OIL; .ALPHA.-TOCOPHEROL ACETATE

NAKED SUNDAYS GLOW BODY MIST SUNSCREEN SPRAY SPF 50 +

ACTIVE INGREDIENT

AVOBENZONE 3% SUNSCREEN

HOMOSALATE 10% SUNSCREEN

OCTISALATE 5 % SUNSCREEN

OCTOCRYLENR 8 % SUNSCREEN

USE

Helps prevent Sunburn

If used as directed with other sun Protection measure (see directions), decrease the risk of skin cancer and early skin ageing caused by the sun

warning

For External use Only

Do not use on damaged or broken skin

When using this product

Keep out of eyes, Rinse with water to remove

stop use and ask a doctor

if rash occurs

Keep Out of reach of children

if Product is swallowed , get medical help or contact a poison control center right away

Directions

Generously spray to exposed areas holding bottle 10-15 cm away from skin. Ensure even application by spraying at least 7 times per section of body until product is visible, Rub in lightly.

Use a water- resistant sunscreen if swimming or sweating.

reapply at least every 2 hours.

Children under 6 months of age : ask a doctor

Inactive Ingredients

alcohol, Citrullius Lanatus Seed oil, Kakadu Plum, Tocopheryl Acetate, Fragrance

other information

Protect the product in this container from excessive heat & direct sun

Sun Protection Measures

Spending time in the Sun Increases your risk of skin cancer and early skin ageing. To decrease this risk , regularly use a sunscreen with a Broad Spectrum SPF value of 15 or higher and other sun protection Measures including:

Limit time in the sun, especially from 10.00 AM - 2.00 PM

Wea long-sleeved Shirts , pants hats, and sunglasses,

PURPOSE

Sunscreen